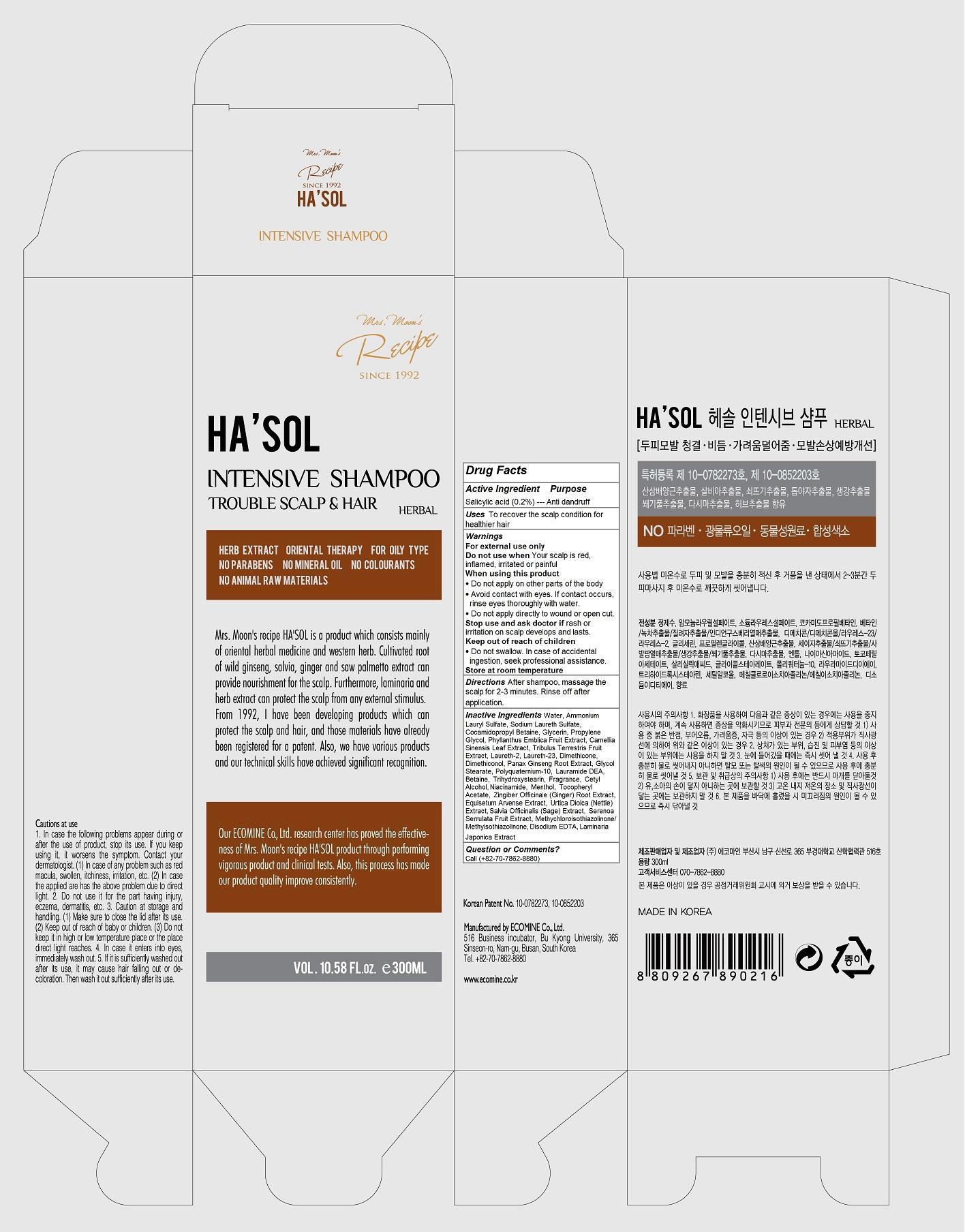 DRUG LABEL: HASOL Intensive
NDC: 51270-119 | Form: SHAMPOO
Manufacturer: Ecomine Co., Ltd.
Category: otc | Type: HUMAN OTC DRUG LABEL
Date: 20140818

ACTIVE INGREDIENTS: SALICYLIC ACID 0.1 1/300 mL
INACTIVE INGREDIENTS: NIACINAMIDE; WATER; AMMONIUM LAURYL SULFATE; SODIUM LAURETH SULFATE; COCAMIDOPROPYL BETAINE; GLYCERIN; PROPYLENE GLYCOL; PHYLLANTHUS EMBLICA FRUIT; GREEN TEA LEAF; TRIBULUS TERRESTRIS FRUIT; LAURETH-2; LAURETH-23; DIMETHICONE; DIMETHICONOL (100000 CST); ASIAN GINSENG; GLYCOL STEARATE; POLYQUATERNIUM-10 (1000 MPA.S AT 2%); LAURIC DIETHANOLAMIDE; BETAINE; TRIHYDROXYSTEARIN; CETYL ALCOHOL; MENTHOL; .ALPHA.-TOCOPHEROL ACETATE; GINGER; EQUISETUM ARVENSE BRANCH; URTICA DIOICA LEAF; SALVIA OFFICINALIS WHOLE; SAW PALMETTO; METHYLCHLOROISOTHIAZOLINONE; EDETATE DISODIUM; LAMINARIA JAPONICA

HA'SOL Intensive Shampoo